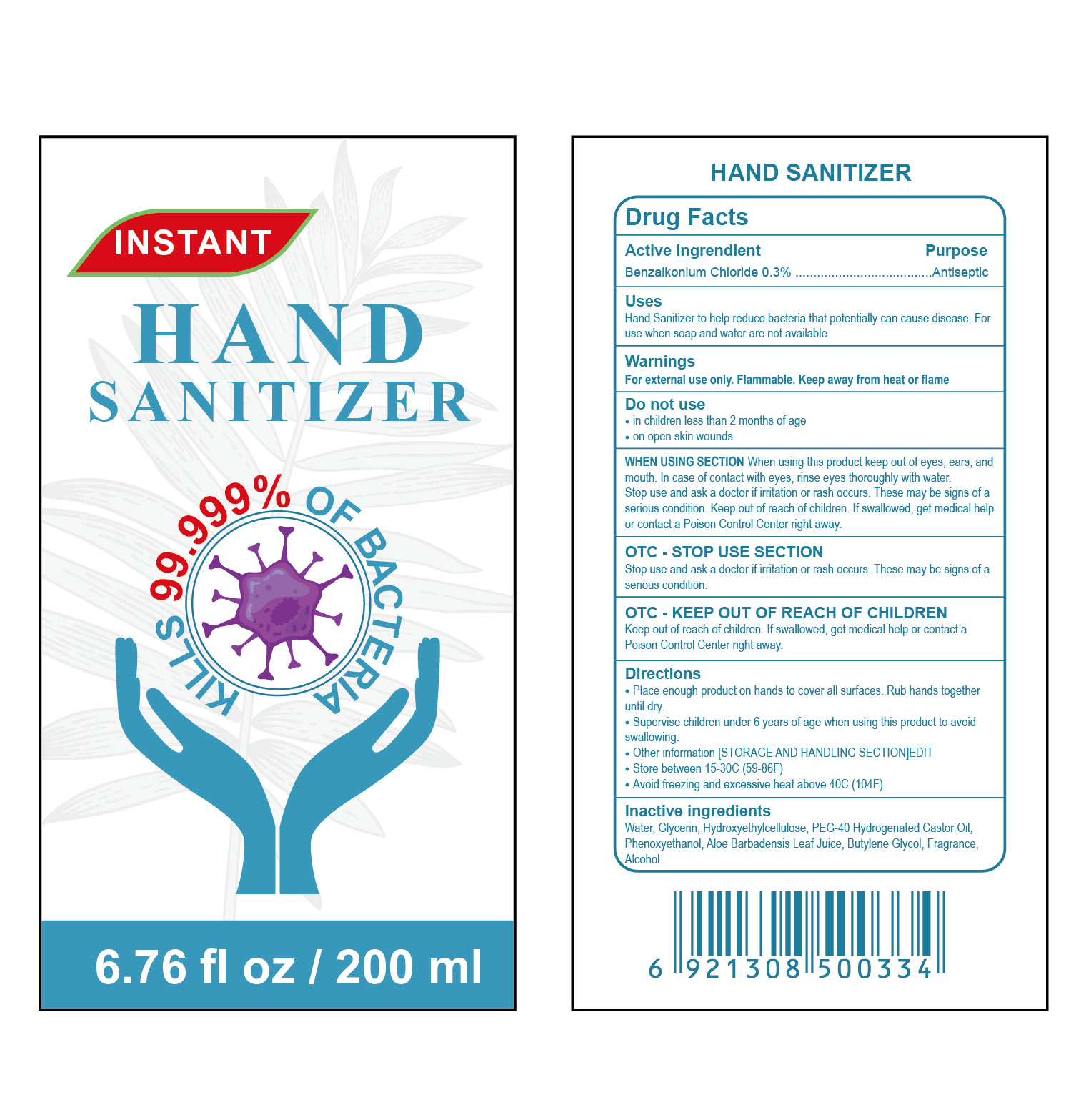 DRUG LABEL: HAND SANITIZER
NDC: 76526-005 | Form: GEL
Manufacturer: Xiamen Cleanss Daily Chemical Co.，Ltd.
Category: otc | Type: HUMAN OTC DRUG LABEL
Date: 20200510

ACTIVE INGREDIENTS: BENZALKONIUM CHLORIDE 0.3 g/100 mL
INACTIVE INGREDIENTS: POLYOXYL 40 HYDROGENATED CASTOR OIL; ALOE VERA LEAF; WATER; PHENOXYETHANOL; BUTYLENE GLYCOL DICAPRYLATE; HYDROCHLORIC ACID

Purpose

Purpose Antiseptic

WHEN USING SECTION

When using this product keep out of eyes, ears, and mouth. In case of contact with eyes, rinse eyes thoroughly with water Stop use and ask a doctor if irritation or rash occurs. These may be signs of a serous condition. Keep out of reach of children. If swallowed, get medical help or contact a Poison Control Center right away

Active ingrendient Benzalkonium Chloride 0.3%

OTC- KEEP OUT OF REACH OF CHILDREN

Keep out of reach of children. If swallowed, get medical help or contact a Poison Control Center right away

Use

Uses Hand Sanitizer to help reduce bacteria that potentially can cause disease. Foruse when soap and water are not available

Warnings

Warnings For external use only. Flammable. Keep away from heat or flame

Do not use section

in children less than 2 months of ageon open skin wounds

Other information STORAGE AND HANDLING SECTIONJEDITStore between 15-30C(59-86P)Avoid freezing and excessive heat ab

Directions

Place enough product on hands to cover all surfaces. Rub hands togetheruntil drySupervise children under 6 years of age when using this product to avoidngOther information STORAGE AND HANDLING SECTIONJEDITStore between 15-30C(59-86P)Avoid freezing and excessive heat above 40C(104P)

INACTIVE INGREDIENT

Water, Glycerin, Hydroxyethylcellulose, PEG-40 Hydrogenated Castor OilPhenoxyethanol, Aloe Barbadensis Leaf Juice, Butylene Glycol, Fragrance